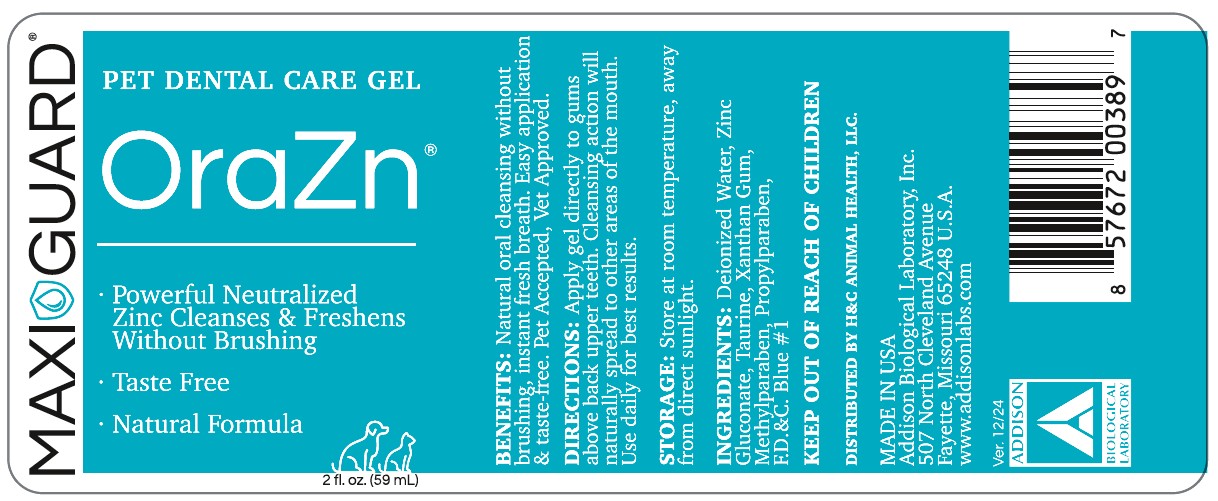 DRUG LABEL: OraZn
NDC: 86137-6509 | Form: GEL
Manufacturer: H&C Animal Health
Category: animal | Type: OTC ANIMAL DRUG LABEL
Date: 20251201

ACTIVE INGREDIENTS: ZINC GLUCONATE 0.022 g/1 mL
INACTIVE INGREDIENTS: WATER; TAURINE; METHYLPARABEN; PROPYLPARABEN; FD&C BLUE NO. 1

H&C Maxi Guard OraZn

INFORMATION FOR OWNERS/CAREGIVERS

Benefits: Natural oral cleansing without brushing, instant fresh breath, Easy application & taste free. Pet Accepted, Vet Approved.

INSTRUCTIONS FOR USE

Directions: Apply gel directly to gums above the back upper teeth. Cleansing action will naturally spread to other areas of the mouth. Use daily for best results.

STORAGE AND HANDLING

Storage: Store at room temperature and keep out of direct sunlight.

ACTIVE INGREDIENT

Ingredients: Ingredients: Deionized Water, Zinc Gluconate, Taurine, Xanthan Gum Methylparaben, Propylparaben, F.D.&C. Blue #1.

Keep out of reach of children.

DISTRIBUTED BY H&C ANIMAL HEALTH, LLC.

MADE IN THE U.S.A.

Addison Biological Laboratory, Inc.

507 North Cleveland Avenue

Fayette, Missouri 65248 U.S.A.

www.addisonlabs.com

Rev. 12/24

Principal Display Panel - OraZn

PET DENTAL CARE GEL
OraZn®

• Powerful Neutralized Zinc Cleanses & Freshens
Without Brushing
• Taste Free
• Natural Formula
2 FL. OZ (59mL)

Benefits: Natural oral cleansing without brushing, instant fresh breath, Easy application & taste free. Pet Accepted, Vet Approve
Directions: Apply gel directly to gums above the back upper teeth. Cleansing action will naturally spread to other areas of the mouth. Use daily for best results.
Storage: Store at room temperature and keep out of direct sunlight.
Ingredients: Deionized Water, Zinc Gluconate, Taurine, Xanthan Gum Methylparaben, Propylparaben, F.D.&C. Blue #1.

Keep out of reach of children.

DISTRIBUTED BY H&C ANIMAL HEALTH, LLC.
MADE IN THE U.S.A.
Addison Biological Laboratory, Inc.
507 North Cleveland Avenue
Fayette, Missouri 65248 U.S.A.
www.addisonlabs.com
Rev. 12/24